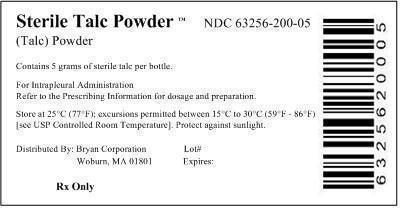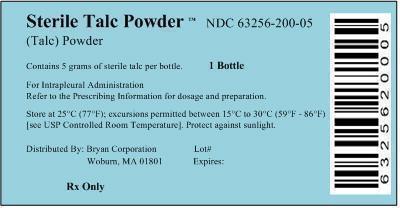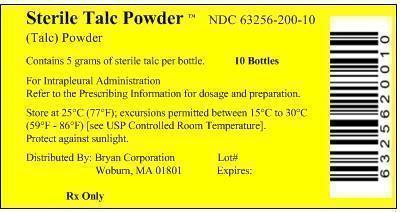 DRUG LABEL: Sterile Talc
NDC: 63256-200 | Form: POWDER
Manufacturer: Bryan Corporation
Category: prescription | Type: HUMAN PRESCRIPTION DRUG LABEL
Date: 20140605

ACTIVE INGREDIENTS: Talc 5 g/100 mL

HIGHLIGHTS OF PRESCRIBING INFORMATION

These highlights do not include all the information needed to use STERILE TALC POWDER safely and effectively. See full prescribing information for STERILE TALC POWDER.
STERILE TALC POWDER (talc), for intrapleural use Initial U.S. Approval: 2003

1 INDICATIONS AND USAGE

STERILE TALC POWDER is a sclerosing agent indicated to decrease the recurrence of malignant pleural effusions in symptomatic patients following maximal drainage of the pleural effusion. (1)

2 DOSAGE AND ADMINISTRATION

- The recommended dose is 5 g, dissolved in 50 ml to 100 ml 0.9% Sodium Chloride Injection, USP , administered intrapleurally (2.1)
- Prepare and administer suspension as recommended (2.2)

3 DOSAGE FORMS AND STRENGTHS

5 g powder in a single-dose bottle, for suspension (3)

4 CONTRAINDICATIONS

None. (4)

5 WARNINGS AND PRECAUTIONS

- Pneumonitis and Acute Respiratory Distress Syndrome (ARDS): Acute Pneumonitis and ARDS, including fatal cases, occur with intrapleural talc administration. (5.1)
- Interference with Future Procedures: Sclerosis of the pleural space may preclude or complicate subsequent ipsilateral surgery and diagnostic procedures. (5.2)

6 ADVERSE REACTIONS

Commonly observed adverse reactions are fever and pain. (6)

To report SUSPECTED ADVERSE REACTIONS, contact Bryan Corporation at 1-800-343-7711 or FDA at 1-800-FDA-1088 or www.fda.gov/medwatch

FULL PRESCRIBING INFORMATION

1 INDICATIONS AND USAGE

Sterile Talc Powder is indicated to decrease the recurrence of malignant pleural effusions in symptomatic patients following maximal drainage of the pleural effusion.

2 DOSAGE AND ADMINISTRATION

2.1 Recommended Dose

The recommended dose is 5 g, suspended in 50 ml to 100 ml 0.9% Sodium Chloride Injection, USP

2.2 Preparation

Prepare the talc suspension using aseptic technique in an appropriate laminar flow hood as follows:

Step 1. Using a 16 gauge needle attached to a 60-ml LuerLok syringe, draw up 50 ml of 0.9 % Sodium Chloride injection, USP. Vent the talc bottle using a needle. Slowly inject the 50 ml of 0.9% Sodium Chloride Injection, USP into the bottle.

Step 2. Swirl the bottle to disperse the talc powder.

Step 3. Divide the contents of the bottle equally into two 60 ml LuerLok syringes, each attached with a 16 gauge needle, by withdrawing 25 ml of the suspension into each syringe with continuous swirling. Add 0.9% Sodium Chloride Injection, USP to a total volume of 50 ml in each syringe. Draw 10 ml of air into each syringe to the 60 ml mark to serve as a headspace for mixing prior to administration. Each syringe should contain 2.5 g of Sterile Talc Powder in 50 ml of 0.9% Sodium Chloride Injection, USP with an air headspace of 10 ml.

Step 4. Label the syringes with the talc concentration, the expiration date and time, the identity of the patient intended to receive the material, and the following statements:

“SHAKE SYRINGE WELL to resuspend before administration”

“FOR PLEURODESIS ONLY – not for intravenous administration”

Step 5. If not used immediately, store prepared suspension in refrigerator. Discard the prepared suspension if not used within 12 hours.

2.3 Administration

Prior to administration, continuously agitate the syringes to evenly redisperse the talc and avoid settlement. Immediately prior to administration, vent the 10 ml air headspace from each syringe. Administer the talc suspension through the chest tube according to standard procedures.

3 DOSAGE FORMS AND STRENGTHS

5 gram white or off-white to light gray sterile powder for suspension in a single-dose glass bottle.

4 CONTRAINDICATIONS

None

5 WARNINGS AND PRECAUTIONS

5.1 Pneumonitis and Acute Respiratory Distress Syndrome (ARDS)

Acute Pneumonitis and ARDS, including fatal cases, occur with intrapleural talc administration.

5.2 Interference with Future Procedures

Sclerosis of the pleural space may preclude or complicate subsequent ipsilateral surgery and diagnostic procedures. Consider the possible effects of the use of Sterile Talc Powder on future diagnostic and therapeutic procedures prior to administration.

6 ADVERSE REACTIONS

Common adverse reactions observed with intrapleurally-administered talc are fever and pain. Other adverse reactions include dyspnea, arrhythmia, empyema, and acute respiratory distress syndrome.

8 USE IN SPECIFIC POPULATIONS

8.1 Pregnancy

Pregnancy Category B.

Risk Summary

A reproduction study performed in rabbits at doses up to approximately 5 times the human dose revealed no evidence of teratogenicity. There are no adequate and well-controlled studies in pregnant women. Because animal reproduction studies are not always predictive of human response, this drug should be used during pregnancy only if clearly needed.

Animal Data

Rabbits were administered talc by oral gavage daily during the period of organogenesis at doses of up to 900 mg/kg (approximately 5 times the human dose on a mg/m^2 basis). No significant dose-related toxicity was reported except at maternally toxic doses. In multiple animal studies, intrapleurally administered talc was not absorbed systemically.

8.4 Pediatric Use

Safety and effectiveness have not been established in pediatric patients.

11 DESCRIPTION

STERILE TALC POWDER is a sclerosing agent for intrapleural administration. STERILE TALC POWDER is white or off-white to light gray, asbestos-free and brucite-free sterile talc powder of controlled particle size. The powder is ≥ 95% hydrated magnesium silicate [Mg3Si4O10 (OH)2, molecular weight 379.3]; associated minerals include chlorite (hydrated aluminum and magnesium silicate), dolomite (calcium and magnesium carbonate), calcite (calcium carbonate), and quartz. Talc is insoluble in water.

12 CLINICAL PHARMACOLOGY

12.1 Mechanism of Action

Talc instilled into the pleural cavity is thought to result in an inflammatory reaction. This reaction can promote adherence of the visceral and parietal pleura, which may prevent reaccumulation of pleural fluid.

13 NONCLINICAL TOXICOLOGY

13.1 Carcinogenesis, Mutagenesis, Impairment of Fertility

Studies on the carcinogenicity of talc have been performed using non-standard designs which prevent firm conclusions on its carcinogenicity. With single intraperitoneal administration to mice at 20 mg and observation for at least 6 months or 4 weekly doses administered intraperitoneally at 25 mg/dose to rats with observation for at least 84 weeks, tumor incidence was not increased. In these studies the talc and its asbestos content were not characterized.

Genotoxicity was tested in cultures of rat pleural mesothelial cells (RPMC) as unscheduled DNA synthesis (UDS) and sister chromatid exchanges (SCEs). None of the talc samples (which were asbestos-free) induced enhancement of UDS or SCEs in treated cultures. No information is available on impairment of fertility in animals by talc.

16 HOW SUPPLIED/STORAGE AND HANDLING

STERILE TALC POWDER is supplied in a single use 100 ml brown glass bottle, sealed with a gray, 20 mm stopper and covered with a flip-off seal.

NDC 63256-200-05: 5 gram individual bottle packaged in a pouch.

NDC 63256-200-10: Carton of ten (10) 5-gram bottles.

Store the powder at 25°C (77°F); excursions permitted between15°C to 30°C (59°F - 86°F) [see USP Controlled Room Temperature]. Protect against sunlight.

17 PATIENT COUNSELING INFORMATION

Advise patients to notify their healthcare provider if new or worsening pulmonary symptoms develop [see Warnings and Precautions (5.1)].

Distributed by:
Bryan Corporation. Woburn, MA 01801.

Principal Display Panel - Bottle Label

Sterile Talc Powder™

(Talc) Powder

Contains 5 grams of sterile talc per bottle

For Intrapleural Administration
Refer to the Prescribing Information for dosage and preparation.

Store at 25°C (77°F); excursions permitted between 15°C to 30°C (59°F - 86°F)
[see USP Controlled Room Temperature]. Protect against sunlight.

Distributed By: Bryan Corporation Lot#
Woburn, MA 01801 Expired:

Rx Only

Principal Display Panel - Pouch Label

Sterile Talc Powder™ NDC 63256-200-05

(Talc) Powder

Contains 5 grams of sterile talc per bottle 1 Bottle

For Intrapleural Administration
Refer to the Prescribing Information for dosage and preparation.

Store at 25°C (77°F); excursions permitted between 15°C to 30°C (59°F - 86°F)
[see USP Controlled Room Temperature]. Protects against sunlight.

Distributed By: Bryan Corporation Lot#
Woburn, MA 01801 Expired:

Rx Only

Principal Display Panel - Box Label

Sterile Talc Powder™ NDC 63256-200-10

(Talc) Powder

Contains 5 grams of sterile talc per bottle 10 Bottles

For Intrapleural Administration
Refer to the Prescribing Information for dosage and preparation.

Store at 25°C (77°F); excursions permitted between 15°C to 30°C
(59°F - 86°F) [see USP Controlled Room Temperature].

Distributed By: Bryan Corporation Lot#
Woburn, MA 01801 Expired:

Rx Only